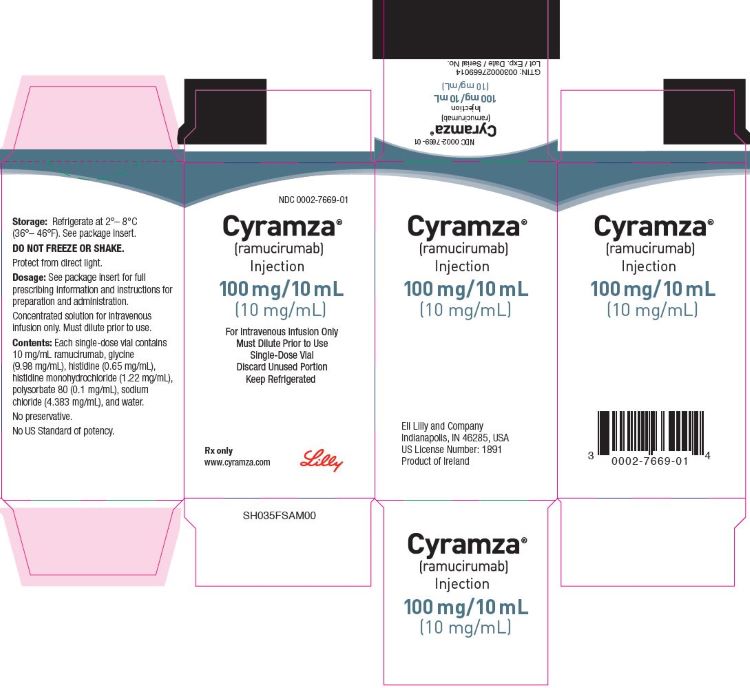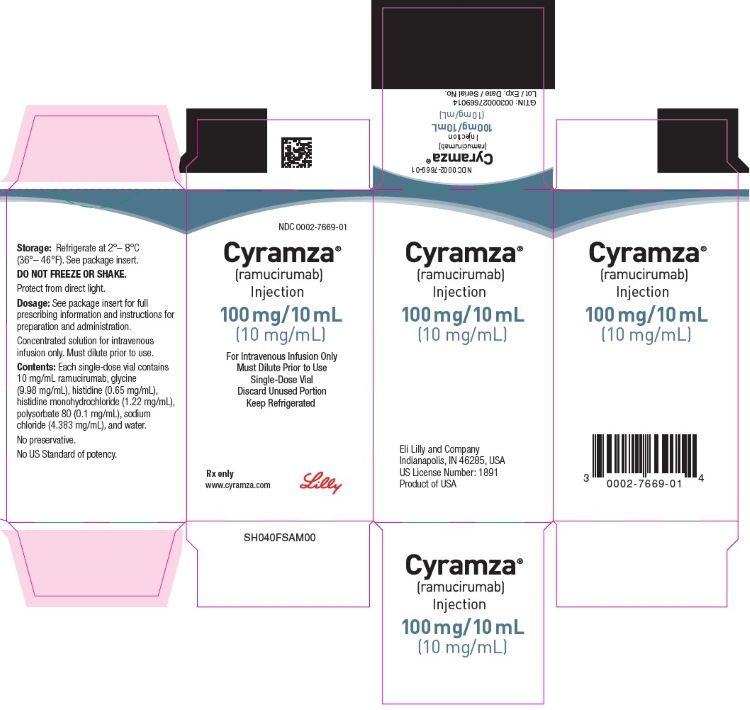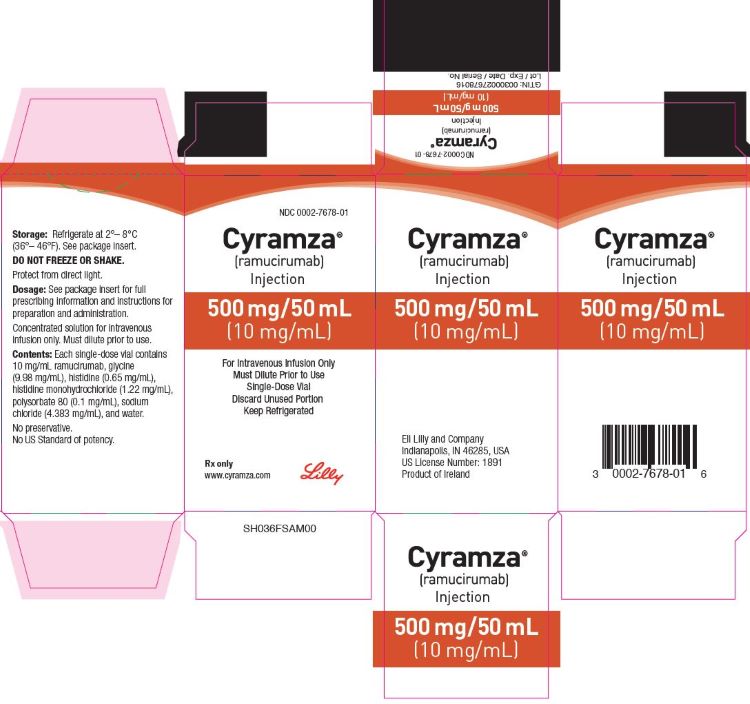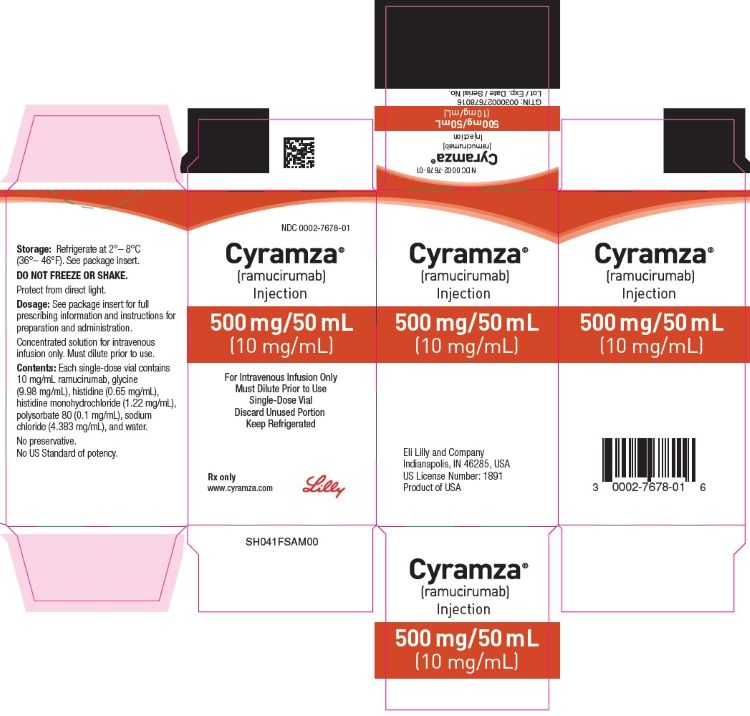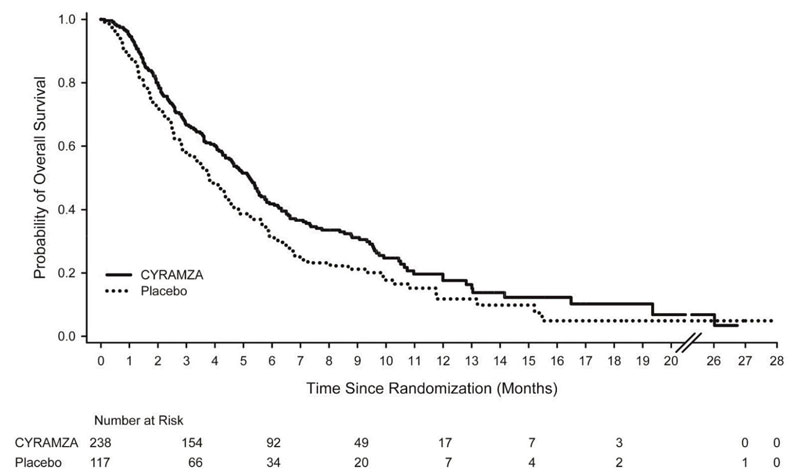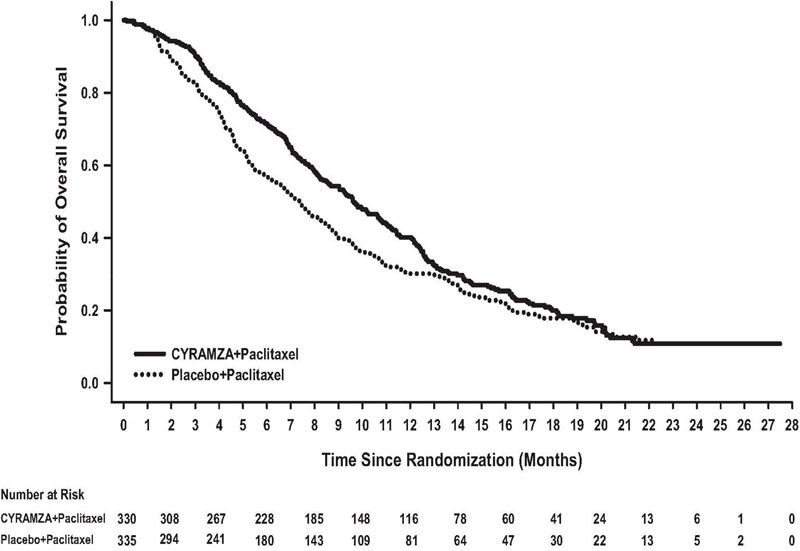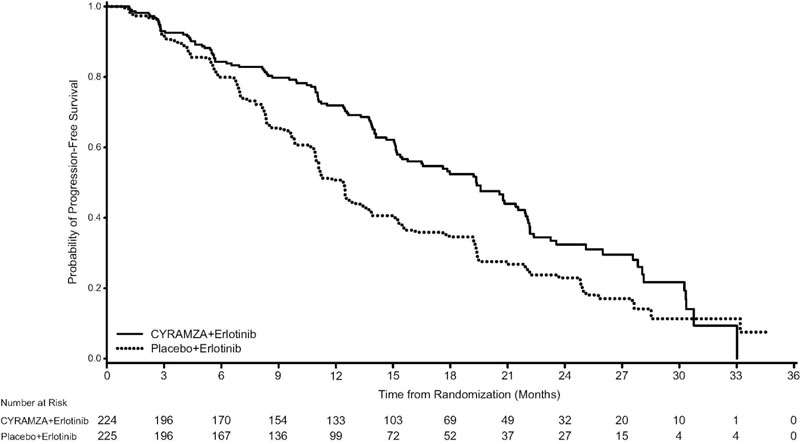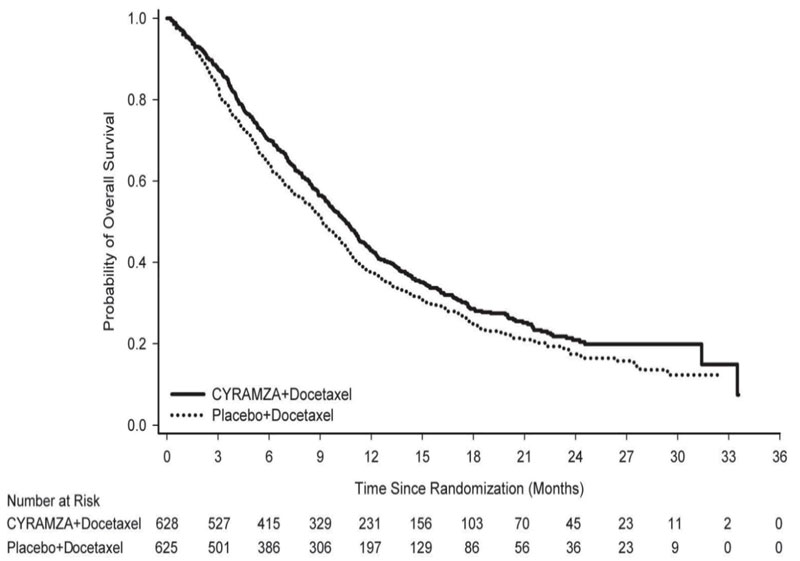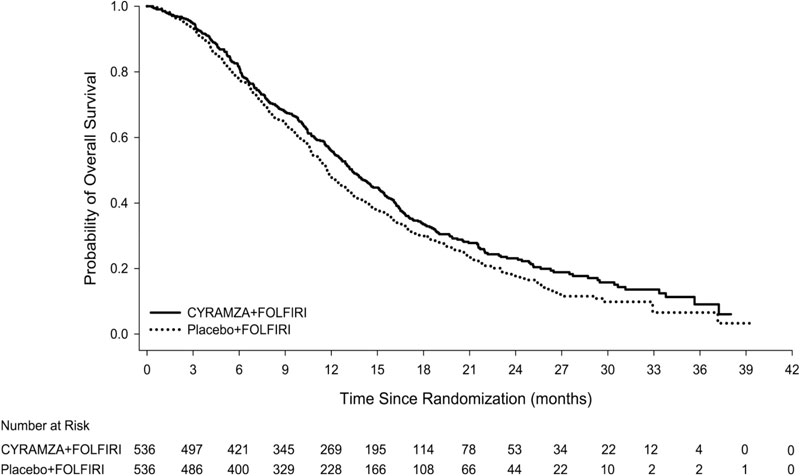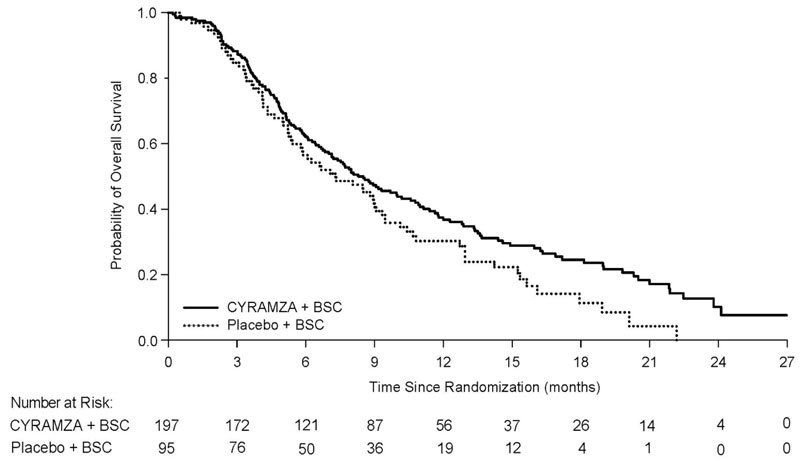 DRUG LABEL: CYRAMZA
NDC: 0002-7669 | Form: SOLUTION
Manufacturer: Eli Lilly and Company
Category: prescription | Type: HUMAN PRESCRIPTION DRUG LABEL
Date: 20251218

ACTIVE INGREDIENTS: ramucirumab 10 mg/1 mL
INACTIVE INGREDIENTS: histidine 0.65 mg/1 mL; histidine monohydrochloride 1.22 mg/1 mL; sodium chloride 4.38 mg/1 mL; glycine 9.98 mg/1 mL; polysorbate 80 0.1 mg/1 mL; water

HIGHLIGHTS OF PRESCRIBING INFORMATION

These highlights do not include all the information needed to use CYRAMZA safely and effectively. See full prescribing information for CYRAMZA.
CYRAMZA (ramucirumab) injection, for intravenous use
Initial U.S. Approval: 2014

1 INDICATIONS AND USAGE

CYRAMZA® is a human vascular endothelial growth factor receptor 2 (VEGFR2) antagonist indicated:

- as a single agent or in combination with paclitaxel, for treatment of adults with advanced or metastatic gastric or gastro-esophageal junction adenocarcinoma with disease progression on or after prior fluoropyrimidine- or platinum-containing chemotherapy. (1.1)
- in combination with erlotinib, for first-line treatment of adults with metastatic non-small cell lung cancer with epidermal growth factor receptor (EGFR) exon 19 deletions or exon 21 (L858R) mutations. (1.2)
- in combination with docetaxel, for treatment of adults with metastatic non-small cell lung cancer with disease progression on or after platinum-based chemotherapy. Patients with EGFR or ALK genomic tumor aberrations should have disease progression on FDA-approved therapy for these aberrations prior to receiving CYRAMZA. (1.2)
- in combination with FOLFIRI, for the treatment of adults with metastatic colorectal cancer with disease progression on or after prior therapy with bevacizumab, oxaliplatin, and a fluoropyrimidine. (1.3)
- as a single agent, for the treatment of adults with hepatocellular carcinoma in patients who have an alpha fetoprotein of ≥400 ng/mL and have been treated with sorafenib. (1.4)

2 DOSAGE AND ADMINISTRATION

- For intravenous infusion only. Do not administer as an intravenous push or bolus. (2.7)
- Premedicate before each infusion. (2.1)
- Gastric Cancer: Administer CYRAMZA 8 mg/kg every 2 weeks as a single agent or in combination with weekly paclitaxel. (2.2)
- Non-Small Cell Lung Cancer:
  - Administer CYRAMZA 10 mg/kg every 2 weeks with daily erlotinib. (2.3)
  - Administer CYRAMZA 10 mg/kg on Day 1 of a 21-day cycle prior to docetaxel. (2.3)
- Colorectal Cancer: Administer CYRAMZA 8 mg/kg every 2 weeks prior to FOLFIRI. (2.4)
- Hepatocellular Carcinoma: Administer CYRAMZA 8 mg/kg every 2 weeks. (2.5)

3 DOSAGE FORMS AND STRENGTHS

Injection: 100 mg/10 mL (10 mg/mL) or 500 mg/50 mL (10 mg/mL) solution in a single-dose vial (3)

4 CONTRAINDICATIONS

None (4)

5 WARNINGS AND PRECAUTIONS

- Hemorrhage: CYRAMZA increases the risk of hemorrhage and gastrointestinal hemorrhage, including severe and fatal events. Permanently discontinue CYRAMZA in patients who experience severe bleeding. (5.1)
- Gastrointestinal Perforations: CYRAMZA increases the risk of gastrointestinal perforation, which can be fatal. Permanently discontinue CYRAMZA in patients who experience a gastrointestinal perforation. (5.2)
- Impaired Wound Healing: Withhold CYRAMZA for 28 days prior to elective surgery. Do not administer CYRAMZA for at least 2 weeks following a major surgical procedure and until adequate wound healing. The safety of resumption of CYRAMZA after resolution of wound healing complications has not been established. (5.3)
- Arterial Thromboembolic Events (ATEs): Serious and sometimes fatal ATEs can occur with CYRAMZA. Permanently discontinue CYRAMZA in patients who experience an ATE. (5.4)
- Hypertension: Monitor blood pressure and treat hypertension. Withhold CYRAMZA for severe hypertension. Permanently discontinue CYRAMZA for hypertension that cannot be controlled with antihypertensive therapy and for hypertensive crisis or hypertensive encephalopathy. (5.5)
- Infusion-Related Reactions (IRR): Monitor for signs and symptoms during infusion. Reduce the infusion rate for Grade 1 or 2 IRR and permanently discontinue for Grade 3 or 4 IRR. (5.6)
- Worsening of Pre-existing Hepatic Impairment: New onset or worsening encephalopathy, ascites or hepatorenal syndrome can occur in patients with Child-Pugh B or C cirrhosis. (5.7)
- Posterior Reversible Encephalopathy Syndrome: Permanently discontinue CYRAMZA. (5.8)
- Proteinuria Including Nephrotic Syndrome: Monitor for proteinuria. Withhold CYRAMZA for urine protein levels greater than or equal to 2 g per 24 hours. Permanently discontinue CYRAMZA for urine protein levels greater than 3 g per 24 hours or nephrotic syndrome. (5.9)
- Thyroid Dysfunction: Monitor thyroid function during treatment. (5.10)
- Embryo-Fetal Toxicity: Can cause fetal harm. Advise females of reproductive potential of the potential risk to a fetus and to use effective contraception. (5.11, 8.1, 8.3)

6 ADVERSE REACTIONS

- The most common adverse reactions observed in single agent CYRAMZA-treated gastric cancer patients at a rate of ≥10% and ≥2% higher than placebo were hypertension and diarrhea. (6.1)
- The most common adverse reactions observed in patients treated with CYRAMZA with paclitaxel at a rate of ≥30% and ≥2% higher than placebo with paclitaxel were fatigue/asthenia, neutropenia, diarrhea, and epistaxis. (6.1)
- The most common adverse reactions observed in patients treated with CYRAMZA with erlotinib at a rate of ≥30% and ≥2% higher than placebo with erlotinib were, infections, hypertension, stomatitis, proteinuria, alopecia, and epistaxis. The most common laboratory abnormalities at a rate of ≥30% and ≥2% higher difference in incidence between arms were increased alanine aminotransferase, increased aspartate aminotransferase, anemia, thrombocytopenia, and neutropenia. (6.1)
- The most common adverse reactions observed in patients treated with CYRAMZA with docetaxel at a rate of ≥30% and ≥2% higher than placebo with docetaxel were neutropenia, fatigue/asthenia, and stomatitis/mucosal inflammation. (6.1)
- The most common adverse reactions observed in patients treated with CYRAMZA with FOLFIRI at a rate of ≥30% and ≥2% higher than placebo with FOLFIRI were diarrhea, neutropenia, decreased appetite, epistaxis, and stomatitis. (6.1)
- The most common adverse reactions observed in single agent CYRAMZA-treated HCC patients at a rate of ≥15% and ≥2% higher than placebo were fatigue, peripheral edema, hypertension, abdominal pain, decreased appetite, proteinuria, nausea, and ascites. The most common laboratory abnormalities at a rate of ≥30% and a ≥2% higher difference in incidence between arms were thrombocytopenia, hypoalbuminemia, and hyponatremia. (6.1)

To report SUSPECTED ADVERSE REACTIONS, contact Eli Lilly and Company at 1-800-LillyRx (1-800-545-5979) or FDA at 1-800-FDA-1088 or www.fda.gov/medwatch.

8 USE IN SPECIFIC POPULATIONS

- Lactation: Advise not to breastfeed. (8.2)

FULL PRESCRIBING INFORMATION

1 INDICATIONS AND USAGE

1.1 Gastric Cancer

CYRAMZA®, as a single agent or in combination with paclitaxel, is indicated for the treatment of adults with advanced or metastatic, gastric or gastro-esophageal junction (GEJ) adenocarcinoma with disease progression on or after prior fluoropyrimidine- or platinum-containing chemotherapy.

1.2 Non-Small Cell Lung Cancer

CYRAMZA, in combination with erlotinib, is indicated for the first-line treatment of adults with metastatic non-small cell lung cancer (NSCLC) whose tumors have epidermal growth factor receptor (EGFR) exon 19 deletions or exon 21 (L858R) substitution mutations.

CYRAMZA, in combination with docetaxel, is indicated for the treatment of adults with metastatic non-small cell lung cancer (NSCLC) with disease progression on or after platinum-based chemotherapy. Patients with epidermal growth factor receptor (EGFR) or anaplastic lymphoma kinase (ALK) genomic tumor aberrations should have disease progression on FDA-approved therapy for these aberrations prior to receiving CYRAMZA.

1.3 Colorectal Cancer

CYRAMZA, in combination with FOLFIRI (irinotecan, folinic acid, and fluorouracil), is indicated for the treatment of adults with metastatic colorectal cancer (mCRC) with disease progression on or after prior therapy with bevacizumab, oxaliplatin, and a fluoropyrimidine.

1.4 Hepatocellular Carcinoma

CYRAMZA, as a single agent, is indicated for the treatment of adults with hepatocellular carcinoma (HCC) who have an alpha fetoprotein (AFP) of ≥400 ng/mL and have been treated with sorafenib.

2 DOSAGE AND ADMINISTRATION

2.1 Premedication

- Prior to each CYRAMZA infusion, premedicate all patients with an intravenous histamine-1 receptor antagonist (e.g., diphenhydramine hydrochloride) [see Warnings and Precautions (5.6)].
- For patients who have experienced a Grade 1 or 2 IRR, premedicate with a histamine-1 receptor antagonist, dexamethasone (or equivalent), and acetaminophen prior to each CYRAMZA infusion [see Dosage and Administration (2.6)].

2.2 Recommended Dosage for Gastric Cancer

- The recommended dosage of CYRAMZA, either as a single agent or in combination with weekly paclitaxel, is 8 mg/kg every 2 weeks administered by intravenous infusion over 60 minutes. If the first infusion is tolerated, all subsequent CYRAMZA infusions may be administered over 30 minutes. Continue CYRAMZA until disease progression or unacceptable toxicity.
- When given in combination with paclitaxel, administer CYRAMZA prior to administration of paclitaxel.
- Refer to the prescribing information for paclitaxel for dosage information.

2.3 Recommended Dosage for Non-Small Cell Lung Cancer

EGFR Exon 19 Deletions or Exon 21 (L858R) Substitution Mutations – CYRAMZA in Combination with Erlotinib

- The recommended dosage of CYRAMZA is 10 mg/kg every 2 weeks administered by intravenous infusion over 60 minutes. If the first infusion is tolerated, all subsequent CYRAMZA infusions may be administered over 30 minutes. Continue CYRAMZA until disease progression or unacceptable toxicity.
- Refer to the prescribing information for erlotinib for dosage information.

Disease Progression On Or After Platinum-based Chemotherapy – CYRAMZA in Combination with Docetaxel

- The recommended dosage of CYRAMZA is 10 mg/kg administered by intravenous infusion over 60 minutes on Day 1 of a 21-day cycle prior to docetaxel infusion. If the first infusion is tolerated, all subsequent CYRAMZA infusions may be administered over 30 minutes. Continue CYRAMZA until disease progression or unacceptable toxicity.
- Refer to the prescribing information for docetaxel for dosage information.

2.4 Recommended Dosage for Colorectal Cancer

- The recommended dosage of CYRAMZA is 8 mg/kg every 2 weeks administered by intravenous infusion over 60 minutes prior to FOLFIRI administration. If the first infusion is tolerated, all subsequent CYRAMZA infusions may be administered over 30 minutes. Continue CYRAMZA until disease progression or unacceptable toxicity.
- Refer to the prescribing information for fluorouracil, leucovorin, and irinotecan for dosage information.

2.5 Recommended Dosage for Hepatocellular Carcinoma

- The recommended dosage of CYRAMZA is 8 mg/kg every 2 weeks administered by intravenous infusion over 60 minutes. If the first infusion is tolerated, all subsequent CYRAMZA infusions may be administered over 30 minutes. Continue CYRAMZA until disease progression or unacceptable toxicity.

2.6 Dosage Modifications for Adverse Reactions

Reduce dose, withhold dose, or discontinue CYRAMZA to manage adverse reactions as described in Table 1.

Table 1: Dosage Modifications for CYRAMZA
Adverse Reaction | Severitya | Dosage Modification
Hemorrhage [see Warnings and Precautions (5.1)] | Grade 3 or 4 | Permanently discontinue CYRAMZA
Gastrointestinal Perforation [see Warnings and Precautions (5.2)] | All Grades | Permanently discontinue CYRAMZA
Wound Healing Complications [see Warnings and Precautions (5.3)] | All Grades | - Withhold CYRAMZA for 28 days prior to elective surgery. Resume CYRAMZA no sooner than 2 weeks after surgery and until adequate wound healing. - The safety of resumption of CYRAMZA after resolution of wound healing complications has not been established.
Arterial Thromboembolic Events [see Warnings and Precautions (5.4)] | All Grades | Permanently discontinue CYRAMZA
Hypertension [see Warnings and Precautions (5.5)] | Severe hypertension | Withhold CYRAMZA until controlled with medical management
Hypertension [see Warnings and Precautions (5.5)] | Severe hypertension that cannot be controlled with antihypertensive therapy | Permanently discontinue CYRAMZA
Infusion-Related Reaction (IRR) [see Dosage and Administration (2.1), Warnings and Precautions (5.6)] | Grade 1 or 2 IRR | Reduce the infusion rate of CYRAMZA by 50%
Infusion-Related Reaction (IRR) [see Dosage and Administration (2.1), Warnings and Precautions (5.6)] | Grade 3 or 4 IRR | Permanently discontinue CYRAMZA
Posterior Reversible Encephalopathy Syndrome (PRES) [see Warnings and Precautions (5.8)] | All Grades | Permanently discontinue CYRAMZA
Proteinuria [see Warnings and Precautions (5.9)] | First occurrence of increased urine protein levels greater than or equal to 2 g per 24 hours | - Withhold CYRAMZA until urine protein level is less than 2 g per 24 hours - Resume CYRAMZA at a reduced dose: - Reduce 8 mg/kg dose to 6 mg/kg - Reduce 10 mg/kg dose to 8 mg/kg
Proteinuria [see Warnings and Precautions (5.9)] | Reoccurrence of urine protein level greater than 2 g per 24 hours following initial dose reduction | - Withhold CYRAMZA until urine protein level is less than 2 g per 24 hours - Resume CYRAMZA at a reduced dose: - Reduce 6 mg/kg dose to 5 mg/kg - Reduce 8 mg/kg dose to 6 mg/kg
Proteinuria [see Warnings and Precautions (5.9)] | Urine protein level greater than 3 g per 24 hours or in the setting of nephrotic syndrome | Permanently discontinue CYRAMZA
a National Cancer Institute Common Toxicity Criteria for Adverse Events (NCI CTCAE) version 4.0 used to identify adverse reactions

2.7 Preparation and Administration

Preparation

- Visually inspect vials for particulate matter and discoloration. Discard if particulate matter or discolorations are identified.
- Calculate the dose and the required volume of CYRAMZA needed for the calculated dose.
- Withdraw the required volume of CYRAMZA and further dilute with only 0.9% Sodium Chloride Injection in an intravenous infusion container to a final volume of 250 mL. Do not use dextrose containing solutions.
- Do not shake. Gently invert the container to ensure adequate mixing.
- Do not dilute with other solutions or co-infuse with other electrolytes or medications.
- Do not freeze. Store diluted solution for no more than 24 hours at 2°C to 8°C (36°F to 46°F) or 4 hours at room temperature (below 25°C [77°F]).
- Discard any unused portion of CYRAMZA.

Administration

- Visually inspect the diluted solution for particulate matter and discoloration prior to administration. Discard if particulate matter or discolorations are identified.
- Do not administer CYRAMZA as an intravenous push or bolus.
- Administer diluted CYRAMZA solution via infusion pump through a separate infusion line. Use of a protein sparing 0.22 micron filter is recommended.
- Flush the line with sterile 0.9% Sodium Chloride Injection at the end of the infusion.

3 DOSAGE FORMS AND STRENGTHS

Injection: 100 mg/10 mL (10 mg/mL) or 500 mg/50 mL (10 mg/mL) clear to slightly opalescent, colorless to slightly yellow solution in a single-dose vial

4 CONTRAINDICATIONS

None

5 WARNINGS AND PRECAUTIONS

5.1 Hemorrhage

CYRAMZA increased the risk of hemorrhage and gastrointestinal hemorrhage, including Grade ≥3 hemorrhagic events. Across six clinical studies in 2137 patients with various cancers treated with CYRAMZA, the incidence of all Grade hemorrhage ranged from 13-55%. Grade 3-5 hemorrhage incidence ranged from 2-5% [see Adverse Reactions (6.1)].

Patients with gastric cancer receiving nonsteroidal anti-inflammatory drugs (NSAIDs) were excluded from enrollment in REGARD and RAINBOW; therefore, the risk of gastric hemorrhage in CYRAMZA-treated patients with gastric tumors receiving NSAIDs is unknown.

Patients with NSCLC receiving therapeutic anticoagulation or with evidence of major airway invasion by cancer were excluded from REVEL. In addition, patients with NSCLC with a recent history of gross hemoptysis, those receiving chronic therapy with NSAIDs or other anti-platelet therapy other than once daily aspirin, or with radiographic evidence of major blood vessel invasion or intratumor cavitation were excluded from REVEL and RELAY; therefore, the risk of pulmonary hemorrhage in these groups of patients is unknown.

Permanently discontinue CYRAMZA in patients who experience severe (Grade 3 or 4) bleeding [see Dosage and Administration (2.6)].

5.2 Gastrointestinal Perforations

CYRAMZA can increase the risk of gastrointestinal perforation, a potentially fatal event. Across six clinical studies in 2137 patients with various cancers treated with CYRAMZA, the incidence of all Grade and Grade 3-5 gastrointestinal perforations ranged from <1-2% [see Adverse Reactions (6.1)].

Permanently discontinue CYRAMZA in patients who experience a gastrointestinal perforation [see Dosage and Administration (2.6)].

5.3 Impaired Wound Healing

Impaired wound healing can occur in patients who receive drugs that inhibit the VEGF or VEGFR pathway. CYRAMZA, a VEGFR2 antagonist, has the potential to adversely affect wound healing. CYRAMZA has not been studied in patients with serious or non-healing wounds.

Withhold CYRAMZA for 28 days prior to elective surgery. Do not administer CYRAMZA for at least 2 weeks following a major surgical procedure and until adequate wound healing. The safety of resumption of CYRAMZA after resolution of wound healing complications has not been established [see Dosage and Administration (2.6)].

5.4 Arterial Thromboembolic Events

Serious, sometimes fatal, arterial thromboembolic events (ATEs), including myocardial infarction, cardiac arrest, cerebrovascular accident, and cerebral ischemia, occurred across clinical trials. Across six clinical studies in 2137 patients with various cancers treated with CYRAMZA, the incidence of all Grade ATE was 1-3%. Grade 3-5 ATE incidence was <1-2% [see Adverse Reactions (6.1)].

Permanently discontinue CYRAMZA in patients who experience an ATE [see Dosage and Administration (2.6)].

5.5 Hypertension

An increased incidence of severe hypertension occurred in patients receiving CYRAMZA. Across five clinical studies, excluding RELAY, in 1916 patients with various cancers treated with CYRAMZA, the incidence of all Grade hypertension ranged from 11-26%. Grade 3-5 hypertension incidence ranged from 6-15% [see Adverse Reactions (6.1)]. In 221 patients with NSCLC receiving CYRAMZA in combination with erlotinib in the RELAY study, the incidence of new or worsening hypertension was higher (45%), as was the incidence of Grade 3-5 hypertension (24%). Of the patients experiencing new or worsening hypertension in RELAY (N=100 CYRAMZA and erlotinib; N=27 placebo and erlotinib), 13% of those treated with CYRAMZA and erlotinib required initiation of 3 or more antihypertensive medications compared to 4% of patients treated with placebo and erlotinib.

Control hypertension prior to initiating treatment with CYRAMZA. Monitor blood pressure every two weeks or more frequently as indicated during treatment. Withhold CYRAMZA for severe hypertension until medically controlled. Permanently discontinue CYRAMZA for medically significant hypertension that cannot be controlled with antihypertensive therapy or in patients with hypertensive crisis or hypertensive encephalopathy [see Dosage and Administration (2.6)].

5.6 Infusion-Related Reactions

Infusion-related reactions (IRR), including severe and life-threatening IRR, occurred in CYRAMZA clinical trials. The majority of IRR across trials occurred during or following a first or second CYRAMZA infusion. Symptoms of IRR included rigors/tremors, back pain/spasms, chest pain and/or tightness, chills, flushing, dyspnea, wheezing, hypoxia, and paresthesia. In severe cases, symptoms included bronchospasm, supraventricular tachycardia, and hypotension. Across six clinical studies in 2137 patients with various cancers treated with CYRAMZA in which premedication was recommended or required, the incidence of all Grade IRR ranged from <1-9%. Grade 3-5 IRR incidence was <1% [see Adverse Reactions (6.1)].

Premedicate prior to each CYRAMZA infusion [see Dosage and Administration (2.1)]. Monitor patients during the infusion for signs and symptoms of IRR in a setting with available resuscitation equipment. Reduce the infusion rate by 50% for Grade 1-2 IRR. Permanently discontinue CYRAMZA for Grade 3-4 IRR [see Dosage and Administration (2.6)].

5.7 Worsening of Pre-existing Hepatic Impairment

Clinical deterioration, manifested by new onset or worsening encephalopathy, ascites, or hepatorenal syndrome, was reported in patients with Child-Pugh B or C cirrhosis who received single agent CYRAMZA. Use CYRAMZA in patients with Child-Pugh B or C cirrhosis only if the potential benefits of treatment are judged to outweigh the risks of clinical deterioration.

Based on safety data from REACH-2, in patients with Child-Pugh A liver cirrhosis, the pooled incidence of hepatic encephalopathy and hepatorenal syndrome was higher for patients who received CYRAMZA (6%) compared to patients who received placebo (0%) [see Adverse Reactions (6.1)].

5.8 Posterior Reversible Encephalopathy Syndrome

Posterior Reversible Encephalopathy Syndrome (PRES) (also known as Reversible Posterior Leukoencephalopathy Syndrome [RPLS]) has been reported in <0.1% of 2137 patients enrolled in six clinical studies with CYRAMZA. Symptoms of PRES include seizure, headache, nausea/vomiting, blindness, or altered consciousness, with or without associated hypertension.

Confirm the diagnosis of PRES with magnetic resonance imaging and permanently discontinue CYRAMZA in patients who develop PRES. Symptoms may resolve or improve within days, although some patients with PRES can experience ongoing neurologic sequelae or death [see Dosage and Administration (2.6)].

5.9 Proteinuria Including Nephrotic Syndrome

Across six clinical studies in 2137 patients with various cancers treated with CYRAMZA, the incidence of all Grade proteinuria ranged from 3-34%. Grade ≥3 proteinuria (including 4 patients with nephrotic syndrome) incidence ranged from <1-3% [see Adverse Reactions (6.1)].

Monitor proteinuria by urine dipstick and/or urinary protein creatinine ratio. If the result of the urine dipstick is 2+ or greater, perform a 24-hour urine collection for protein measurement. Withhold CYRAMZA for urine protein levels that are 2 or more grams over 24 hours. Reinitiate CYRAMZA at a reduced dose once the urine protein level returns to less than 2 grams over 24 hours. Permanently discontinue CYRAMZA for urine protein levels greater than 3 grams over 24 hours or in the setting of nephrotic syndrome [see Dosage and Administration (2.6)].

5.10 Thyroid Dysfunction

Across six clinical studies in 2137 patients with various cancers treated with CYRAMZA, the incidence of Grade 1-2 hypothyroidism ranged from <1-3%; there were no reports of Grade 3-5 hypothyroidism [see Adverse Reactions (6.1)]. Monitor thyroid function during treatment with CYRAMZA.

5.11 Embryo-Fetal Toxicity

Based on its mechanism of action, CYRAMZA can cause fetal harm when administered to pregnant women. Animal models link angiogenesis, VEGF and VEGFR2 to critical aspects of female reproduction, embryo-fetal development, and postnatal development. Advise pregnant women of the potential risk to a fetus. Advise females of reproductive potential to use effective contraception during treatment with CYRAMZA and for 3 months after the last dose [see Use in Specific Populations (8.1, 8.3)].

6 ADVERSE REACTIONS

The following serious adverse reactions are described elsewhere in the labeling:

- Hemorrhage [see Warnings and Precautions (5.1)].
- Gastrointestinal Perforations [see Warnings and Precautions (5.2)].
- Impaired Wound Healing [see Warnings and Precautions (5.3)].
- Arterial Thromboembolic Events [see Warnings and Precautions (5.4)].
- Hypertension [see Warnings and Precautions (5.5)].
- Infusion-Related Reactions [see Warnings and Precautions (5.6)].
- Worsening of Pre-existing Hepatic Impairment [see Warnings and Precautions (5.7)].
- Posterior Reversible Encephalopathy Syndrome [see Warnings and Precautions (5.8)].
- Proteinuria Including Nephrotic Syndrome [see Warnings and Precautions (5.9)].
- Thyroid Dysfunction [see Warnings and Precautions (5.10)].

6.1 Clinical Trials Experience

Because clinical trials are conducted under widely varying conditions, adverse reaction rates observed in the clinical trials of a drug cannot be directly compared to rates in the clinical trials of another drug and may not reflect the rates observed in practice.

The data described in the Warnings and Precautions section reflect exposure to CYRAMZA in 2137 patients from six studies: REGARD, RAINBOW, RAISE, REVEL, REACH-2, and RELAY.

Gastric Cancer

The safety of CYRAMZA was evaluated in REGARD and RAINBOW [see Clinical Studies (14.1)]. Patients in both trials had locally advanced or metastatic gastric cancer (including GEJ adenocarcinoma) and had previously received platinum- or fluoropyrimidine-containing chemotherapy. Patients had Eastern Cooperative Oncology Group (ECOG) performance status (PS) of 0 or 1. Both trials excluded patients with uncontrolled hypertension, major surgery within 28 days, or patients receiving chronic anti-platelet therapy other than once daily aspirin. REGARD excluded patients with bilirubin ≥1.5 mg/dL and RAINBOW excluded patients with bilirubin >1.5 times the upper limit of normal (ULN).

CYRAMZA Administered as a Single Agent (REGARD)

Patients received either CYRAMZA 8 mg/kg or placebo intravenously every two weeks. Patients randomized to CYRAMZA received a median of 4 doses; the median duration of exposure was 8 weeks and 32 (14% of 236) patients received CYRAMZA for at least six months.

The most common serious adverse reactions with CYRAMZA were anemia (3.8%) and intestinal obstruction (2.1%). Red blood cell transfusions were given to 11% of CYRAMZA-treated patients versus 8.7% of patients who received placebo.

The most common adverse reactions (all grades) observed in CYRAMZA-treated patients at a rate of ≥10% and ≥2% higher than placebo were hypertension and diarrhea. Table 2 provides the frequency and severity of adverse reactions (CTCAE, version 4.0) in REGARD.

Table 2: Adverse Reactions Occurring in ≥5% of Patients with a ≥2% Difference Between Arms in REGARD
Adverse Reactions | CYRAMZA (N=236) |  | Placebo (N=115)
Adverse Reactions | All Grades (%) | Grade 3-4 (%) | All Grades (%) | Grade 3-4 (%)
Vascular
Hypertensiona | 16 | 8 | 8 | 3
Gastrointestinal
Diarrhea | 14 | 1 | 9 | 2
Nervous System
Headache | 9 | 0 | 3 | 0
Metabolism and Nutrition
Hyponatremia | 6 | 3 | 2 | 1
a Hypertension is a consolidated term.

Clinically relevant adverse reactions reported in ≥1% and <5% of CYRAMZA-treated patients in REGARD were:

- Neutropenia (4.7%)
- Epistaxis (4.7%)
- Rash (4.2%)
- Intestinal obstruction (2.1%)
- Arterial thromboembolic events (1.7%)

Across clinical trials of CYRAMZA administered as a single agent, clinically relevant adverse reactions (including Grade ≥3) reported in CYRAMZA-treated patients included proteinuria, gastrointestinal perforation, and IRR. In REGARD, according to laboratory assessment, 8% of CYRAMZA-treated patients developed proteinuria versus 3% of placebo-treated patients. Two patients discontinued CYRAMZA due to proteinuria. The rate of gastrointestinal perforation in REGARD was 0.8% and the rate of IRR was 0.4%.

CYRAMZA Administered in Combination with Paclitaxel (RAINBOW)

Patients received paclitaxel 80 mg/m^2 on Days 1, 8, and 15 of each 28-day cycle with either CYRAMZA 8 mg/kg or placebo intravenously every two weeks. Patients randomized to CYRAMZA received a median of 9 doses; the median duration of exposure was 18 weeks, and 93 (28% of 327) patients received CYRAMZA for at least six months.

The most common serious adverse reactions in patients who received CYRAMZA with paclitaxel were neutropenia (3.7%) and febrile neutropenia (2.4%); 19% of patients who received CYRAMZA with paclitaxel received granulocyte colony-stimulating factors.

Adverse reactions resulting in discontinuation of any component of the CYRAMZA with paclitaxel combination in ≥2% of patients in RAINBOW were neutropenia (4%) and thrombocytopenia (3%).

The most common adverse reactions (all grades) observed in patients who received CYRAMZA with paclitaxel at a rate of ≥30% and ≥2% higher than placebo with paclitaxel were fatigue/asthenia, neutropenia, diarrhea, and epistaxis. Table 3 provides the frequency and severity of adverse reactions (CTCAE, version 4.0) in RAINBOW.

Table 3: Adverse Reactions Occurring in ≥5% of Patients with a ≥2% Difference Between Arms in RAINBOW
Adverse Reactions | CYRAMZA + Paclitaxel (N=327) |  | Placebo + Paclitaxel (N=329)
Adverse Reactions | All Grades (%) | Grade ≥ 3 (%) | All Grades (%) | Grade ≥ 3 (%)
General
Fatigue/Asthenia | 57 | 12 | 44 | 6
Peripheral edema | 25 | 2 | 14 | 1
Hematology
Neutropeniaa | 54 | 41 | 31 | 19
Thrombocytopenia | 13 | 2 | 6 | 2
Gastrointestinal
Diarrhea | 32 | 4 | 23 | 2
Stomatitis | 20 | 1 | 7 | 1
Gastrointestinal hemorrhage eventsa,b | 10 | 4 | 6 | 2
Respiratory, Thoracic, and Mediastinal
Epistaxis | 31 | 0 | 7 | 0
Vascular
Hypertensiona | 25 | 15 | 6 | 3
Renal and Urinary
Proteinuriaa | 17 | 1 | 6 | 0
Metabolism and Nutrition
Hypoalbuminemiaa | 11 | 1 | 5 | 1
a Neutropenia, gastrointestinal hemorrhage events, hypertension, proteinuria, and hypoalbuminemia are consolidated terms.
b Includes 1 fatal event in the CYRAMZA arm.

Clinically relevant adverse reactions reported in ≥1% and <5% of patients receiving CYRAMZA with paclitaxel were:

- Sepsis (3.1%), including 5 fatal events
- Gastrointestinal perforations (1.2%), including 1 fatal event

Non-Small Cell Lung Cancer

CYRAMZA Administered in Combination with Erlotinib (RELAY)

The safety of CYRAMZA was evaluated in RELAY [see Clinical Studies (14.2)]. Patients had previously untreated EGFR exon 19 deletion or exon 21 (L858R) substitution mutation-positive metastatic NSCLC. Patients had ECOG PS 0 or 1. RELAY excluded patients with bilirubin greater than the ULN, central nervous system (CNS) metastases, clinically active interstitial lung disease (ILD), uncontrolled hypertension, major surgery within 28 days, radiographic evidence of major blood vessel invasion or encasement by cancer or intra-tumor cavitation, or gross hemoptysis within the preceding 2 months. The study also excluded patients receiving chronic nonsteroidal anti-inflammatory agents (NSAIDs) or anti-platelet therapy other than once daily aspirin.

Patients received either CYRAMZA 10 mg/kg or placebo intravenously every two weeks in combination with erlotinib 150 mg taken orally once daily. Patients randomized to CYRAMZA received a median of 21 doses; the median duration of exposure was 11 months, and 90 (41% of 221) patients received CYRAMZA for at least 12 months.

The most common serious adverse reactions in patients who received CYRAMZA with erlotinib were pneumonia (3.2%), cellulitis (1.8%), and pneumothorax (1.8%). Red blood cell transfusions were given to 3.2% of CYRAMZA-treated patients versus 0 patients who received placebo.

Treatment discontinuation of all study drugs due to adverse reactions occurred in 13% of CYRAMZA with erlotinib-treated patients, with increased alanine aminotransferase (1.4%) and paronychia (1.4%) being the most common. The most common adverse reactions leading to treatment discontinuation of CYRAMZA were proteinuria (8.6%) and hyperbilirubinemia (6%).

The most common adverse reactions (all grades) observed in CYRAMZA with erlotinib-treated patients at a rate of ≥30% of patients and ≥2% higher than placebo with erlotinib-treated patients were infections, hypertension, stomatitis, proteinuria, alopecia, and epistaxis. The most common laboratory abnormalities ≥30% and ≥2% higher than the placebo were increased alanine aminotransferase, increased aspartate aminotransferase, anemia, thrombocytopenia, and neutropenia. Table 4 provides the frequency and severity of adverse reactions (CTCAE, version 4.0) and Table 5 provides the incidence and severity of laboratory abnormalities in RELAY.

Table 4: Adverse Reactions Occurring in ≥5% of Patients with a ≥2% Difference Between Arms in RELAY
Adverse Reactions | CYRAMZA + Erlotinib (N=221) |  | Placebo + Erlotinib (N=225)
Adverse Reactions | All Grades (%) | Grade ≥3 (%) | All Grades (%) | Grade ≥3 (%)
Infections
Infectionsa,b | 81 | 17 | 76 | 7
Vascular
Hypertension | 45 | 24 | 12 | 5
Gastrointestinal
Diarrhea | 70 | 7 | 71 | 1
Stomatitis | 42 | 2 | 36 | 1
Gastrointestinal hemorrhagec | 10 | 1 | 3 | <1
Gingival bleeding | 9 | 0 | 1 | 0
Renal and Urinary
Proteinuriac | 34 | 3 | 8 | 0
Skin and Subcutaneous Tissue
Alopecia | 34 | N/Ad | 20 | N/Ad
Respiratory, Thoracic, and Mediastinal
Epistaxis | 34 | 0 | 12 | 0
Pulmonary hemorrhagec,e | 7 | <1 | 2 | <1
General
Peripheral edema | 23 | <1 | 4 | 0
Nervous System
Headache | 15 | <1 | 7 | 0
Abbreviations: N/A = not applicable.
a Includes all preferred terms that are part of the System Organ Class Infections and Infestations. Most common (≥1%) Grade ≥3 infections and frequencies for CYRAMZA with erlotinib compared to placebo with erlotinib, respectively, include pneumonia (3% versus 0%), cellulitis (1% versus 0%), paronychia (4% versus 3%), skin infection (1% versus 0%), and urinary tract infection (1% versus 0%).
b Includes 3 fatal events in the CYRAMZA arm.
c Gastrointestinal hemorrhage, proteinuria, and pulmonary hemorrhage are consolidated terms.
d Grade ≥3 does not exist in CTCAE.
e Includes 1 fatal event in the CYRAMZA arm.

Table 5: Laboratory Abnormalities Worsening from Baseline in ≥20% (All Grades) of Patients Receiving CYRAMZA with Erlotinib with a Difference Between Arms of ≥2% in RELAY
Laboratory Abnormality |  | CYRAMZA + Erlotiniba |  |  | Placebo + Erlotiniba
 | All Grades (%) |  | Grade ≥3 (%) | All Grades (%) |  | Grade ≥3 (%)
Chemistry
Alanine aminotransferase increased | 74 |  | 11 | 60 |  | 13
Aspartate aminotransferase increased | 71 |  | 6 | 47 |  | 4
Alkaline phosphatase increased | 25 |  | <1 | 16 |  | 1
Hypokalemia | 24 |  | 5 | 18 |  | 2
Hematology
Anemia | 42 |  | 5 | 25 |  | 2
Thrombocytopenia | 41 |  | 3 | 12 |  | 3
Neutropenia | 33 |  | 7 | 21 |  | 4
a The denominator used to calculate the incidence varied based on the number of patients with a baseline and at least one on-study laboratory measurement: CYRAMZA-treated patients (range 215-218 patients) and placebo-treated patients (range 224-225 patients).

CYRAMZA Administered in Combination with Docetaxel (REVEL)

The safety of CYRAMZA was evaluated in REVEL [see Clinical Studies (14.2)]. Patients had NSCLC with disease progression on or after one platinum-based therapy for locally advanced or metastatic disease and ECOG PS 0 or 1. REVEL excluded patients with bilirubin greater than the ULN, uncontrolled hypertension, major surgery within 28 days, radiographic evidence of major airway or blood vessel invasion by cancer, radiographic evidence of intra-tumor cavitation, or gross hemoptysis within the preceding 2 months, and patients receiving therapeutic anticoagulation or chronic anti-platelet therapy other than once daily aspirin.

Patients received either CYRAMZA 10 mg/kg or placebo intravenously in combination with docetaxel 75 mg/m^2 intravenously every 21 days. Due to an increased incidence of neutropenia and febrile neutropenia in patients enrolled in East Asian sites, REVEL was amended and 24 patients (11 patients receiving CYRAMZA with docetaxel, 13 patients receiving placebo with docetaxel) at East Asian sites received a starting dose of docetaxel at 60 mg/m^2 every three weeks. Patients randomized to CYRAMZA received a median of 4.5 doses; the median duration of exposure was 3.5 months, and 195 (31% of 627) patients received CYRAMZA for at least six months.

The most common serious adverse reactions in patients who received CYRAMZA with docetaxel were febrile neutropenia (14%), pneumonia (6%), and neutropenia (5%). The use of granulocyte colony-stimulating factors was 42% in CYRAMZA with docetaxel-treated patients versus 37% in patients who received placebo with docetaxel.

The most common adverse reactions leading to treatment discontinuation of CYRAMZA were IRR (0.5%) and epistaxis (0.3%). For patients with non-squamous histology, the overall incidence of pulmonary hemorrhage was 7% and the incidence of Grade ≥3 pulmonary hemorrhage was 1% for CYRAMZA with docetaxel compared to 6% overall incidence and 1% for Grade ≥3 pulmonary hemorrhage for placebo with docetaxel. For patients with squamous histology, the overall incidence of pulmonary hemorrhage was 10% and the incidence of Grade ≥3 pulmonary hemorrhage was 2% for CYRAMZA with docetaxel compared to 12% overall incidence and 2% for Grade ≥3 pulmonary hemorrhage for placebo with docetaxel. Treatment discontinuation due to adverse reactions occurred more frequently in CYRAMZA with docetaxel-treated patients (9%) than in placebo with docetaxel-treated patients (5%).

The most common adverse reactions (all grades) observed in CYRAMZA with docetaxel-treated patients at a rate of ≥30% and ≥2% higher than placebo with docetaxel were neutropenia, fatigue/asthenia, and stomatitis/mucosal inflammation. Table 6 provides the frequency and severity of adverse reactions (NCI CTCAE, version 4.0) in REVEL.

Table 6: Adverse Reactions Occurring in ≥5% of Patients with a ≥2% Difference Between Arms in REVEL
Adverse Reactions | CYRAMZA + Docetaxel (N=627) |  | Placebo + Docetaxel (N=618)
Adverse Reactions | All Grades (%) | Grade 3-4 (%) | All Grades (%) | Grade 3-4 (%)
Hematology
Neutropeniaa | 55 | 49 | 46 | 40
Febrile neutropenia | 16 | 16 | 10 | 10
Thrombocytopeniaa | 13 | 3 | 5 | <1
General
Fatigue/Asthenia | 55 | 14 | 50 | 11
Peripheral edema | 16 | 0 | 9 | <1
Gastrointestinal
Stomatitis/Mucosal inflammation | 37 | 7 | 19 | 2
Respiratory, Thoracic, and Mediastinal
Epistaxis | 19 | <1 | 7 | <1
Eye
Lacrimation increased | 13 | <1 | 5 | 0
Vascular
Hypertensiona | 11 | 6 | 5 | 2
a Neutropenia, thrombocytopenia, and hypertension are consolidated terms.

Clinically relevant adverse drug reactions reported in ≥1% and <5% of CYRAMZA with docetaxel-treated patients in REVEL were:

- Hyponatremia (4.8%)
- Proteinuria (3.3%)

Colorectal Cancer

The safety of CYRAMZA was evaluated in RAISE [see Clinical Studies (14.3)]. Patients had mCRC with disease progression on or after therapy with bevacizumab, oxaliplatin, and a fluoropyrimidine and ECOG PS 0 or 1. RAISE excluded patients with uncontrolled hypertension, major surgery within 28 days, and those who experienced any of the following during first-line therapy with a bevacizumab-containing regimen: an arterial thrombotic/thromboembolic event; Grade 4 hypertension; Grade 3 proteinuria; a Grade 3-4 bleeding event; or bowel perforation.

Patients received either CYRAMZA 8 mg/kg or placebo intravenously in combination with FOLFIRI intravenously every two weeks. Patients randomized to CYRAMZA received a median of 8 doses (range 1-68); the median duration of exposure was 4.4 months, and 169 (32% of 529) patients received CYRAMZA for at least six months.

The most common serious adverse reactions with CYRAMZA with FOLFIRI were diarrhea (3.6%), intestinal obstruction (3.0%), and febrile neutropenia (2.8%).

Treatment discontinuation of any study drug due to adverse reactions occurred more frequently in CYRAMZA with FOLFIRI-treated patients (29%) than in placebo with FOLFIRI-treated patients (13%). The most common adverse reactions leading to discontinuation of any component of CYRAMZA with FOLFIRI as compared to placebo with FOLFIRI were neutropenia (12.5% versus 5.3%) and thrombocytopenia (4.2% versus 0.8%). The most common adverse reactions leading to treatment discontinuation of CYRAMZA were proteinuria (1.5%) and gastrointestinal perforation (1.7%).

The most common adverse reactions (all grades) observed in CYRAMZA with FOLFIRI-treated patients at a rate of ≥30% and ≥2% higher than placebo with FOLFIRI were diarrhea, neutropenia, decreased appetite, epistaxis, and stomatitis. Twenty percent of patients treated with CYRAMZA with FOLFIRI received granulocyte colony-stimulating factors. Table 7 provides the frequency and severity of adverse reactions (CTCAE, version 4.0) in RAISE.

Table 7: Adverse Reactions Occurring in ≥5% of Patients with a ≥2% Difference Between Arms in RAISE
Adverse Reactions | CYRAMZA + FOLFIRI (N=529) |  | Placebo + FOLFIRI (N=528)
Adverse Reactions | All Grades (%) | Grade ≥ 3 (%) | All Grades (%) | Grade ≥ 3 (%)
Gastrointestinal
Diarrhea | 60 | 11 | 51 | 10
Decreased appetite | 37 | 2 | 27 | 2
Stomatitis | 31 | 4 | 21 | 2
Gastrointestinal hemorrhage eventsa,b | 12 | 2 | 7 | 1
Hematology
Neutropeniaa | 59 | 38 | 46 | 23
Thrombocytopeniaa | 28 | 3 | 14 | <1
Respiratory, Thoracic, and Mediastinal
Epistaxis | 33 | 0 | 15 | 0
Vascular
Hypertensiona | 26 | 11 | 9 | 3
General
Peripheral edema | 20 | <1 | 9 | 0
Renal and Urinary
Proteinuriaa,c | 17 | 3 | 5 | <1
Skin and Subcutaneous Tissue
Palmar-plantar erythrodysesthesia syndrome | 13 | 1 | 5 | <1
Metabolism and Nutrition
Hypoalbuminemiaa | 6 | 1 | 2 | 0
a Gastrointestinal hemorrhage events, neutropenia, thrombocytopenia, hypertension, proteinuria, and hypoalbuminemia, are consolidated terms.
b Includes 3 fatal events in the CYRAMZA arm.
c Includes 3 patients with nephrotic syndrome in the CYRAMZA arm.

Clinically relevant adverse reactions reported in ≥1% and <5% of patients receiving CYRAMZA with FOLFIRI were:

- Gastrointestinal perforation (1.7%) including 4 fatal events

Thyroid stimulating hormone (TSH) levels were evaluated in 224 patients (115 CYRAMZA with FOLFIRI-treated patients and 109 placebo with FOLFIRI-treated patients) with normal baseline TSH levels. Patients underwent periodic TSH laboratory assessments until 30 days after the last dose of study treatment. Increased TSH levels were observed in 53 (46%) patients treated with CYRAMZA with FOLFIRI compared with 4 (4%) patients treated with placebo with FOLFIRI.

Hepatocellular Carcinoma

The safety of CYRAMZA was evaluated in REACH-2 [see Clinical Studies (14.4)]. Patients had Barcelona Clinic Liver Cancer (BCLC) stage B HCC who were no longer amenable to locoregional therapy, or BCLC stage C HCC, Child-Pugh score A, and baseline AFP ≥400 ng/mL. Patients had ECOG PS 0 or 1. REACH-2 excluded patients with clinically meaningful ascites, history of or current hepatic encephalopathy, uncontrolled hypertension, major surgery within 28 days, bilirubin >1.5 times ULN, severe variceal bleeding in the 3 months prior to treatment or with varices at high risk of bleeding, and patients receiving therapeutic anticoagulation or chronic anti-platelet therapy other than once daily aspirin.

Patients received either CYRAMZA 8 mg/kg or placebo intravenously every two weeks. Patients received a median of 6 doses (range 1-51) of CYRAMZA; the median duration of exposure was 12 weeks (range 2-107 weeks) and 48 patients (24% of 197) received CYRAMZA for at least six months.

The most common serious adverse reactions with CYRAMZA were ascites (3%) and pneumonia (3%).

Treatment discontinuations due to adverse reactions occurred in 18% of CYRAMZA-treated patients, with proteinuria being the most frequent (2%).

The most common adverse reactions reported in ≥15% of patients and ≥2% higher than placebo were fatigue, peripheral edema, hypertension, abdominal pain, decreased appetite, proteinuria, nausea, and ascites. The most common laboratory abnormalities ≥30% and ≥2% higher than placebo were thrombocytopenia, hypoalbuminemia, and hyponatremia. Table 8 provides the frequency and severity of adverse reactions (CTCAE, version 4.0) and Table 9 provides the incidence and severity of laboratory abnormalities in REACH-2.

Table 8: Adverse Reactions Occurring in ≥10% of Patients with a ≥2% Difference Between Arms in REACH-2
Adverse Reactions | CYRAMZA (N=197) |  | Placebo (N=95)
Adverse Reactions | All Grades (%) | Grade ≥ 3 (%) | All Grades (%) | Grade ≥ 3 (%)
General
Fatiguea | 36 | 5 | 20 | 3
Peripheral edema | 25 | 2 | 14 | 0
Decreased appetite | 23 | 2 | 20 | 1
Insomnia | 11 | 0 | 6 | 1
Pyrexia | 10 | 0 | 3 | 0
Vascular
Hypertensiona | 25 | 13 | 13 | 5
Gastrointestinal
Abdominal Paina | 25 | 2 | 16 | 2
Nausea | 19 | 0 | 12 | 0
Ascitesb | 18 | 4 | 7 | 1
Vomiting | 10 | 0 | 7 | 0
Renal and Urinary
Proteinuriaa,c | 20 | 2 | 4 | 0
Nervous System
Headache | 14 | 0 | 5 | 1
Respiratory, Thoracic, and Mediastinal
Epistaxis | 14 | <1 | 3 | 0
Musculoskeletal
Back Pain | 10 | <1 | 7 | 1
a Fatigue, hypertension, abdominal pain, and proteinuria are consolidated terms.
b Includes 1 fatal event in the CYRAMZA arm.
c Includes 1 patient with nephrotic syndrome in the CYRAMZA arm.

Clinically relevant adverse drug reactions reported in ≥1% and <10% of CYRAMZA-treated patients in REACH-2 were:

- IRR (9%)
- Hepatic encephalopathy (5%) including 1 fatal event
- Hepatorenal syndrome (2%) including 1 fatal event

Table 9: Laboratory Abnormalities Worsening from Baseline in ≥15% (All Grades) of Patients Receiving CYRAMZA with a Difference Between Arms of ≥2% in REACH-2
Laboratory Abnormalitya | CYRAMZAb |  | Placebob
Laboratory Abnormalitya | All Grades (%) | Grade ≥ 3 (%) | All Grades (%) | Grade ≥ 3 (%)
Hematology
Thrombocytopenia | 46 | 8 | 15 | 1
Neutropenia | 24 | 8 | 12 | 3
Chemistry
Hypoalbuminemia | 33 | <1 | 16 | 0
Hyponatremia | 32 | 16 | 25 | 5
Hypocalcemia | 16 | 2 | 5 | 0
a Laboratory abnormalities were not included if the ≥ Grade 3 percentage was less than placebo-treated patients.
b The denominator used to calculate the incidence varied based on the number of patients with a baseline and at least one on study laboratory measurement: CYRAMZA-treated patients (range 179-193 patients) and placebo-treated patients (range 84-92 patients).

6.2 Immunogenicity

As with all therapeutic proteins, there is the potential for immunogenicity. The detection of antibody formation is highly dependent on the sensitivity and specificity of the assay. Additionally, the observed incidence of antibody (including neutralizing antibody) positivity in an assay may be influenced by several factors including assay methodology, sample handling, timing of sample collection, concomitant medications, and underlying disease. For these reasons, comparison of incidence of antibodies to CYRAMZA with the incidences of antibodies to other products may be misleading.

In clinical trials, 86/2890 (3%) of CYRAMZA-treated patients tested positive for treatment-emergent anti-ramucirumab antibodies by an enzyme-linked immunosorbent assay (ELISA). Neutralizing antibodies were detected in 14 of the 86 patients who tested positive for treatment-emergent anti-ramucirumab antibodies.

6.3 Postmarketing Experience

The following adverse reactions have been identified during post-approval use of CYRAMZA. Because such reactions are reported voluntarily from a population of uncertain size, it is not always possible to reliably estimate their frequency or establish a causal relationship to drug exposure.

- Blood and lymphatic system: Thrombotic microangiopathy
- Neoplasms benign, malignant and unspecified: Hemangioma
- Respiratory, thoracic, and mediastinal: Dysphonia
- Vascular: Arterial (including aortic) aneurysms, dissections, and rupture
- Cardiac: Heart failure

8 USE IN SPECIFIC POPULATIONS

8.1 Pregnancy

Risk Summary

Based on its mechanism of action [see Clinical Pharmacology (12.1)], CYRAMZA can cause fetal harm when administered to a pregnant woman. There are no available data on CYRAMZA use in pregnant women. Animal models link angiogenesis, VEGF and VEGFR2 to critical aspects of female reproduction, embryo-fetal development, and postnatal development. No animal studies have been conducted to evaluate the effect of ramucirumab on reproduction and fetal development. Advise a pregnant woman of the potential risk to a fetus.

In the U.S. general population, the estimated background risk of major birth defects and miscarriage in clinically recognized pregnancies is 2-4% and 15-20%, respectively.

Data

Animal Data

No animal studies have been specifically conducted to evaluate the effect of ramucirumab on reproduction and fetal development. In mice, loss of the VEGFR2 gene resulted in embryo-fetal death and these fetuses lacked organized blood vessels and blood islands in the yolk sac. In other models, VEGFR2 signaling was associated with development and maintenance of endometrial and placental vascular function, successful blastocyst implantation, maternal and feto-placental vascular differentiation, and development during early pregnancy in rodents and non-human primates. Disruption of VEGF signaling has also been associated with developmental anomalies including poor development of the cranial region, forelimbs, forebrain, heart, and blood vessels.

8.2 Lactation

Risk Summary

There is no information on the presence of ramucirumab in human milk or its effects on the breastfed child or on milk production. Human IgG is present in human milk, but published data suggest that breast milk antibodies do not enter the neonatal and infant circulation in substantial amounts. Because of the potential risk for serious adverse reactions in breastfed children from ramucirumab, advise women not to breastfeed during treatment with CYRAMZA and for 2 months after the last dose.

8.3 Females and Males of Reproductive Potential

Pregnancy Testing

Verify the pregnancy status of females of reproductive potential prior to initiating CYRAMZA [see Use in Specific Populations (8.1)].

Contraception

Based on its mechanism of action, CYRAMZA can cause fetal harm when administered to a pregnant woman [see Use in Specific Populations (8.1)].

Females

Advise females of reproductive potential to use effective contraception during treatment with CYRAMZA and for 3 months after the last dose.

Infertility

Females

Advise females of reproductive potential that based on animal data CYRAMZA may impair fertility [see Nonclinical Toxicology (13.1)].

8.4 Pediatric Use

The safety and effectiveness of CYRAMZA in pediatric patients have not been established.

The safety and effectiveness of CYRAMZA were assessed but not established in a single-arm, multicenter, open-label trial [NCT02564198] that included 23 pediatric patients aged 1 year to <17 years with relapsed or refractory solid tumors who received CYRAMZA as a single agent and two multicenter, randomized, controlled trials [NCT04145700 and NCT04145349] that included 16 pediatric patients aged 1 to <17 years with relapsed, recurrent, or progressive desmoplastic small round cell tumors or synovial sarcoma who received CYRAMZA in combination with chemotherapy versus chemotherapy alone. The effect on open tibial growth plates in pediatric patients who received CYRAMZA has not been adequately studied; however, one patient had progressive widening of distal femoral growth plate. No other new safety signals were observed in pediatric patients. The pharmacokinetic (PK) parameters for these pediatric patients who received CYRAMZA as a single agent or in combination was within the range of the values previously observed in adults given the same dose per body weight.

Juvenile Animal Toxicity Data

In animal studies, effects on epiphyseal growth plates were identified. In cynomolgus monkeys, anatomical pathology revealed adverse effects on the epiphyseal growth plate (thickening and osteochondropathy) at all doses tested (5-50 mg/kg). Ramucirumab exposure at the lowest weekly dose tested in the cynomolgus monkey was 0.2 times the exposure in humans at the recommended dose of ramucirumab as a single agent.

8.5 Geriatric Use

Of the 563 CYRAMZA-treated patients in REGARD and RAINBOW, 205 (36%) were 65 and over, while 41 (7%) were 75 and over. No overall differences in safety or effectiveness were observed between these subjects and younger subjects.

Of the 221 patients who received CYRAMZA with erlotinib in RELAY, 119 (54%) were 65 and over, while 29 (13%) were 75 and over. Overall, no clinically meaningful differences in effectiveness were observed between these patients and younger patients. Adverse reactions occurring at a 10% or higher incidence in patients receiving CYRAMZA with erlotinib and with a 10% or greater difference between patients aged 65 or older compared to patients aged less than 65 years were: diarrhea (75% versus 65%), hypertension (50% versus 40%), increased ALT (49% versus 35%), increased AST (49% versus 33%), stomatitis (46% versus 36%), decreased appetite (32% versus 19%), dysgeusia (23% versus 12%), and weight loss (19% versus 6%).

Of the 1253 patients in REVEL, 455 (36%) were 65 and over and 84 (7%) were 75 and over. Of the 627 patients who received CYRAMZA with docetaxel in REVEL, 237 (38%) were 65 and over, while 45 (7%) were 75 and over. In an exploratory subgroup analysis of REVEL, the hazard ratio for overall survival in patients less than 65 years old was 0.74 (95% CI: 0.62, 0.87) and in patients 65 years and over was 1.10 (95% CI: 0.89, 1.36).

Of the 529 patients who received CYRAMZA with FOLFIRI in RAISE, 209 (40%) were 65 and over, while 51 (10%) were 75 and over. Overall, no differences in safety or effectiveness were observed between these subjects and younger subjects.

Of the 197 patients who received CYRAMZA in REACH-2, 95 (48%) were 65 years and over, while 37 (19%) were 75 years and over. Overall, no differences in efficacy were observed between these subjects and younger subjects.

8.6 Hepatic Impairment

No dose adjustment is recommended for patients with mild (total bilirubin within ULN and aspartate aminotransferase [AST] >ULN or total bilirubin >1 to 1.5 times ULN and any AST) or moderate (total bilirubin >1.5 to 3 times ULN and any AST) hepatic impairment. Clinical deterioration was reported in patients with Child-Pugh B or C cirrhosis who received single agent CYRAMZA [see Warnings and Precautions (5.7), Clinical Pharmacology (12.3)].

11 DESCRIPTION

Ramucirumab is a human VEGFR2 antagonist. It is a recombinant human IgG1 monoclonal antibody. Ramucirumab has an approximate molecular weight of 147 kDa. Ramucirumab is produced in genetically engineered mammalian NS0 cells.

CYRAMZA (ramucirumab) injection for intravenous use is a sterile, preservative-free, clear to slightly opalescent and colorless to slightly yellow solution. CYRAMZA is supplied at a concentration of 10 mg/mL in either 100 mg (10 mL) or 500 mg (50 mL) single-dose vials. CYRAMZA is formulated in glycine (9.98 mg/mL), histidine (0.65 mg/mL), histidine monohydrochloride (1.22 mg/mL), polysorbate 80 (0.1 mg/mL), sodium chloride (4.383 mg/mL), and Water for Injection, USP, pH 6.0.

12 CLINICAL PHARMACOLOGY

12.1 Mechanism of Action

Ramucirumab is a VEGFR2 antagonist that specifically binds VEGFR2 and blocks binding of VEGFR ligands, VEGF-A, VEGF-C, and VEGF-D. As a result, ramucirumab inhibits ligand-stimulated activation of VEGFR2, thereby inhibiting ligand-induced proliferation, and migration of human endothelial cells. Ramucirumab inhibited angiogenesis in an in vivo animal model.

12.3 Pharmacokinetics

The pharmacokinetics (PK) of ramucirumab were studied in patients with various cancers over a dose range of 6-12 mg/kg administered every two or three weeks. The PK characteristics of ramucirumab are similar for patients across cancer types based on a population PK analysis. Ramucirumab systemic exposure increased dose proportionally at doses of 8 mg/kg and above and steady state concentrations were achieved at approximately 12 weeks.

Distribution

The mean (% coefficient of variation [CV%]) volume of distribution of ramucirumab at steady-state (Vss) was 5.4 L (15%).

Elimination

The mean (CV%) clearance of ramucirumab was 0.015 L/hour (30%) and the mean elimination half-life was 14 days (20%).

Specific Populations

Age (19-88 years), sex (68% male), race (70% White, 24% Asian), renal impairment (creatinine clearance [CLcr] calculated by Cockcroft-Gault, 15-89 mL/min, mild hepatic impairment (total bilirubin within ULN and AST>ULN or total bilirubin >1 to 1.5 times ULN and any AST), or moderate hepatic impairment (total bilirubin >1.5 to 3 times ULN) had no clinically meaningful effect on the PK of ramucirumab. The effect of severe hepatic impairment (total bilirubin >3 times ULN and any AST) on the PK of ramucirumab is unknown.

Drug Interaction Studies

No clinically meaningful changes in the exposure of either ramucirumab or its concomitant drugs in the approved combinations, including paclitaxel, docetaxel, irinotecan (or its active metabolite, SN-38), and erlotinib were observed in patients with solid tumors.

13 NONCLINICAL TOXICOLOGY

13.1 Carcinogenesis, Mutagenesis, Impairment of Fertility

No animal studies have been performed to test ramucirumab for potential carcinogenicity or genotoxicity.

Inhibition of VEGFR2 signaling in animal models was shown to result in changes to hormone levels critical for pregnancy, and, in monkeys, an increased duration of the follicular cycle. In a 39 week animal study, female monkeys treated with ramucirumab showed dose dependent increases in follicular mineralization of the ovary.

13.2 Animal Toxicology and/or Pharmacology

Adverse effects in the kidney (glomerulonephritis) occurred in monkeys at doses of 16-50 mg/kg (0.7-5.5 times the exposure in humans at the recommended dose of ramucirumab as a single agent).

A single dose of ramucirumab resulting in an exposure approximately 10 times the human exposure at the recommended dose of ramucirumab as a single agent did not significantly impair wound healing in monkeys using a full-thickness incisional model.

14 CLINICAL STUDIES

14.1 Gastric Cancer

REGARD

The efficacy of CYRAMZA was evaluated in REGARD (NCT00917384), a multinational, randomized, double-blind, multicenter study in patients with locally advanced or metastatic gastric cancer (including adenocarcinoma of the GEJ) who previously received platinum- or fluoropyrimidine-containing chemotherapy. Patients were required to have experienced disease progression either within 4 months after the last dose of first-line therapy for locally advanced or metastatic disease or within 6 months after the last dose of adjuvant therapy. Patients were also required to have ECOG PS of 0 or 1. Patients were randomized (2:1) to receive either an intravenous infusion of CYRAMZA 8 mg/kg or placebo every 2 weeks. Randomization was stratified by weight loss over the prior 3 months (≥10% versus <10%), geographic region, and location of the primary tumor (gastric versus GEJ). The major efficacy outcome measure was overall survival (OS). An additional efficacy outcome measure was progression-free survival (PFS).

A total of 355 patients were randomized, 238 to the CYRAMZA-treatment group and 117 to the placebo-treatment group. Baseline demographic and disease characteristics were similar between treatment arms. The median age was 60 years (range 24-87); 70% were men; 77% were White, 16% Asian; 28% had ECOG PS 0 and 72% had ECOG PS 1; 91% had measurable disease; 75% had gastric cancer; and 25% had adenocarcinoma of the GEJ. The majority of patients (85%) experienced disease progression during or following first-line therapy for metastatic disease. Prior chemotherapy for gastric cancer consisted of platinum/fluoropyrimidine combination therapy (81%), fluoropyrimidine-containing regimens without platinum (15%), and platinum-containing regimens without fluoropyrimidine (4%). Patients received a median of 4 doses (range 1-34) of CYRAMZA or a median of 3 doses (range 1-30) of placebo.

Efficacy results are shown in Table 10 and Figure 1.

Table 10: Efficacy Results in REGARD
 | CYRAMZA + BSC N=238 | Placebo + BSC N=117
Overall Survival
Number of deaths (%) | 179 (75%) | 99 (85%)
Median – months (95% CI) | 5.2 (4.4, 5.7) | 3.8 (2.8, 4.7)
Hazard Ratio (95% CI) | 0.78 (0.60, 0.998)
Stratified Log-rank p-value | 0.047
Progression-free Survival
Number of events (%)a | 199 (84%) | 108 (92%)
Median – months (95% CI) | 2.1 (1.5, 2.7) | 1.3 (1.3, 1.4)
Hazard Ratio (95% CI) | 0.48 (0.38, 0.62)
Stratified Log-rank p-value | <0.001
Abbreviations: BSC = best supportive care; CI = confidence interval
a 65 of 199 events in CYRAMZA-treated patients and 31 of 108 events in placebo-treated patients were deaths.

Figure 1: Kaplan-Meier Curves for Overall Survival in REGARD

RAINBOW

The efficacy of CYRAMZA was evaluated in RAINBOW (NCT01170663), a multinational, randomized, double-blind study in patients with locally advanced or metastatic gastric cancer (including adenocarcinoma of the GEJ) who previously received platinum- and fluoropyrimidine-containing chemotherapy. Patients were required to have experienced disease progression during, or within 4 months after the last dose of first-line therapy. Patients were also required to have ECOG PS of 0 or 1. Patients were randomized (1:1) to receive either CYRAMZA 8 mg/kg or placebo as an intravenous infusion every 2 weeks (on Days 1 and 15) of each 28-day cycle. Patients in both arms received paclitaxel 80 mg/m^2 by intravenous infusion on Days 1, 8, and 15 of each 28-day cycle. Prior to administration of each dose of paclitaxel, patients were required to have adequate hematopoietic and hepatic function. The paclitaxel dose was permanently reduced, in increments of 10 mg/m^2, for a maximum of two dose reductions for Grade 4 hematologic toxicity or Grade 3 paclitaxel-related non-hematologic toxicity. Randomization was stratified by geographic region, time to progression from the start of first-line therapy (<6 months versus ≥6 months), and disease measurability. The major efficacy outcome measure was OS. Additional efficacy outcome measures were PFS and overall response rate (ORR).

A total of 665 patients were randomized, 330 to the CYRAMZA-treatment group and 335 to the placebo-treatment group. Baseline demographics and disease characteristics were similar between treatment arms. The median age was 61 years (range: 24-84); 71% were men; 61% were White, 35% Asian; 39% had ECOG PS 0 and 61% had ECOG PS 1; 78% had measurable disease; 79% had gastric cancer; and 21% had adenocarcinoma of the GEJ. Two-thirds of the patients experienced disease progression while on first-line therapy (67%) and 25% of patients received an anthracycline in combination with platinum/fluoropyrimidine combination therapy.

Efficacy results are shown in Table 11 and Figure 2.

Table 11: Efficacy Results in RAINBOW
 | CYRAMZA + Paclitaxel N=330 | Placebo + Paclitaxel N=335
Overall Survival
Number of deaths (%) | 256 (78%) | 260 (78%)
Median – months (95% CI) | 9.6 (8.5, 10.8) | 7.4 (6.3, 8.4)
Hazard Ratio (95% CI) | 0.81 (0.68, 0.96)
Stratified Log-rank p-value | 0.017
Progression-free Survival
Number of events (%)a | 279 (85%) | 296 (88%)
Median – months (95% CI) | 4.4 (4.2, 5.3) | 2.9 (2.8, 3.0)
Hazard Ratio (95% CI) | 0.64 (0.54, 0.75)
Stratified Log-rank p-value | <0.001
Overall Response Rateb
Rate – percent (95% CI) | 28% (23, 33) | 16% (13, 20)
Stratified CMH p-value | <0.001
Abbreviations: CI = confidence interval, CMH = Cochran-Mantel-Haenszel
a 56 of 279 events in CYRAMZA-treated patients and 55 of 296 events in placebo-treated patients were deaths.
b 2 complete responses in CYRAMZA-treated patients and 1 complete response in placebo-treated patients.

Figure 2: Kaplan-Meier Curves for Overall Survival in RAINBOW

14.2 Non-Small Cell Lung Cancer

RELAY

The efficacy of CYRAMZA in combination with erlotinib was evaluated in RELAY (NCT02411448), a multinational, randomized, double-blind, placebo-controlled, multicenter study in patients with previously untreated metastatic non-small cell lung cancer (NSCLC) whose tumors have epidermal growth factor receptor (EGFR) exon 19 deletion or exon 21 (L858R) substitution mutations. Patients in RELAY were required to have measurable disease, ECOG PS of 0 or 1, no central nervous system (CNS) metastases, and no known EGFR T790M mutations at baseline. Patients were randomized (1:1) to receive either CYRAMZA 10 mg/kg or placebo every 2 weeks as an intravenous infusion, in combination with erlotinib 150 mg orally once daily until disease progression or unacceptable toxicity. Randomization was stratified by geographic region (East Asia versus other), gender, EGFR mutation (exon 19 deletion versus exon 21 [L858R] substitution mutation), and local EGFR testing method (therascreen® and cobas® versus other polymerase chain reaction [PCR] and sequencing-based methods). The major efficacy outcome measure was PFS as assessed by the investigator (RECIST v1.1). Additional efficacy outcome measures included OS, ORR, and duration of response (DoR).

A total of 449 patients were randomized, 224 to the CYRAMZA-treatment group and 225 to the placebo-treatment group. Baseline demographics and disease characteristics were similar between treatment arms. The median age was 65 years (range 23-89); 63% of patients were female; 77% were Asian and 22% were White; 52% had ECOG PS 0; 61% were never smokers; 54% had exon 19 mutation deletions, and 45% had exon 21 (L858R) substitution mutations.

Efficacy results are shown in Table 12 and Figure 3.

Table 12: Efficacy Results in RELAY
 | CYRAMZA + Erlotinib N=224 | Placebo + Erlotinib N=225
Progression-free Survival
Number of events (%)a | 122 (55%) | 158 (70%)
Median – months (95% CI) | 19.4 (15.4, 21.6) | 12.4 (11.0, 13.5)
Hazard Ratio (95% CI) | 0.59 (0.46, 0.76)
Stratified Log-rank p-value | <0.0001
Abbreviations: ITT = Intent-to-treat patients, CI = confidence interval, NR = not reached
a 4 of 122 events in CYRAMZA-treated patients and 1 of 158 events in placebo-treated patients were deaths.

Figure 3: Kaplan-Meier Curves for Progression-Free Survival by Investigator Assessment in RELAY

PFS assessment based on a blinded independent radiologic review was similar to the investigator assessment. The treatment effect for PFS was consistent across pre-specified stratification factors. The ORR was 76% (95% CI: 71, 82) in the CYRAMZA in combination with erlotinib arm and 75% (95% CI: 69, 80) in the placebo in combination with erlotinib arm, with median DoR 18.0 months (95% CI: 13.9, 19.8) and 11.1 months (95% CI: 9.7, 12.3), in each arm respectively.

Based on the prespecified final OS analysis conducted after 297 events, the stratified OS HR was 0.98 (95% CI: 0.78 - 1.24), with median OS of 51.1 months (95% CI: 44.8 - 57.3) in the CYRAMZA in combination with erlotinib arm and 46.0 months (95% CI: 43.6 - 53.0) in the placebo in combination with erlotinib arm.

REVEL

The efficacy of CYRAMZA was evaluated in REVEL (NCT01168973), a multinational, randomized, double-blind study in patients with NSCLC with disease progression on or after one platinum-based therapy for locally advanced or metastatic disease. Patients in REVEL were also required to have ECOG PS 0 or 1. Patients were randomized (1:1) to receive either CYRAMZA at 10 mg/kg or placebo by intravenous infusion, in combination with docetaxel at 75 mg/m^2, every 21 days. Sites in East Asia administered a reduced dose of docetaxel at 60 mg/m^2 every 21 days. Patients who discontinued combination therapy because of an adverse reaction attributed to either CYRAMZA/placebo or docetaxel were permitted to continue monotherapy with the other treatment component until disease progression or intolerable toxicity. Randomization was stratified by geographic region, sex, prior maintenance therapy, and ECOG PS. The major efficacy outcome measure was OS. Additional efficacy outcome measures included PFS and ORR.

A total of 1253 patients were randomized, 628 to the CYRAMZA-treatment group and 625 to the placebo-treatment group. Baseline demographics and disease characteristics were similar between treatment arms. The median age was 62 years (range 21-86); 67% were men; 82% were White and 13% were Asian; 32% had ECOG PS 0; 73% had nonsquamous histology and 26% had squamous histology. In addition to platinum chemotherapy (99%), the most common prior therapies were pemetrexed (38%), gemcitabine (25%), taxane (24%), and bevacizumab (14%). Twenty-two percent of patients received prior maintenance therapy. Tumor EGFR status was unknown for the majority of patients (65%). Where tumor EGFR status was known (n=445), 7.4% were positive for EGFR mutation (n=33). No data were collected regarding tumor ALK rearrangement status.

Overall response rate (complete response + partial response) was 23% (95% CI: 20, 26) for CYRAMZA with docetaxel and 14% (95% CI: 11, 17) for placebo with docetaxel, p-value of <0.001. Efficacy results are shown in Table 13 and Figure 4.

Table 13: Efficacy Results in REVEL
 | CYRAMZA + Docetaxel N=628 | Placebo + Docetaxel N=625
Overall Survival
Number of deaths (%) | 428 (68%) | 456 (73%)
Median – months (95% CI) | 10.5 (9.5, 11.2) | 9.1 (8.4, 10.0)
Hazard Ratio (95% CI) | 0.86 (0.75, 0.98)
Stratified Log-rank p-value | 0.024
Progression-free Survival
Number of events (%)a | 558 (89%) | 583 (93%)
Median – months (95% CI) | 4.5 (4.2, 5.4) | 3.0 (2.8, 3.9)
Hazard Ratio (95% CI) | 0.76 (0.68, 0.86)
Stratified Log-rank p-value | <0.001
Abbreviations: CI = confidence interval
a 126 of 558 events in CYRAMZA-treated patients and 109 of 583 events in placebo-treated patients were deaths.

Figure 4: Kaplan-Meier Curves for Overall Survival in REVEL

14.3 Colorectal Cancer

The efficacy of CYRAMZA was evaluated in RAISE (NCT01183780), a multinational, randomized, double-blind study in patients with mCRC, who had disease progression on or after prior therapy with bevacizumab, oxaliplatin, and a fluoropyrimidine. Patients in RAISE were required to have ECOG PS 0 or 1 and to have disease progression within 6 months of the last dose of first-line therapy. Patients were randomized (1:1) to receive either CYRAMZA at 8 mg/kg as an intravenous infusion or placebo, in combination with FOLFIRI: irinotecan 180 mg/m^2 administered intravenously over 90 minutes and folinic acid 400 mg/m^2 administered intravenously simultaneously over 120 minutes; followed by fluorouracil 400 mg/m^2 intravenous bolus over 2 to 4 minutes; followed by fluorouracil 2400 mg/m^2 administered intravenously by continuous infusion over 46 to 48 hours. Treatment cycles on both arms were repeated every 2 weeks. Patients who discontinued one or more components of treatment because of an adverse reaction were permitted to continue therapy with the other treatment component(s) until disease progression or unacceptable toxicity. Randomization was stratified by geographic region, tumor KRAS status, and time to disease progression after beginning first-line treatment (<6 months versus ≥6 months). The major efficacy outcome measure was OS. An additional efficacy outcome measure was PFS.

A total of 1072 patients were randomized, 536 to the CYRAMZA-treatment group and 536 to the placebo-treatment group. Baseline demographics and disease characteristics were similar between treatment arms. The median age was 62 years (range 21-87); 57% were men; 76% were White and 20% were Asian; 49% had ECOG PS 0; 49% had KRAS mutant tumors; and 24% had <6 months from time to disease progression after beginning first-line treatment. The treatment effect was consistent across the pre-specified stratification factors.

Efficacy results are shown in Table 14 and Figure 5.

Table 14: Efficacy Results in RAISE
 | CYRAMZA + FOLFIRI N=536 | Placebo + FOLFIRI N=536
Overall Survival
Number of deaths (%) | 372 (69%) | 397 (74%)
Median – months (95% CI) | 13.3 (12.4, 14.5) | 11.7 (10.8, 12.7)
Hazard Ratio (95% CI) | 0.85 (0.73, 0.98)
Stratified Log-rank p-value | 0.023
Progression-free Survival
Number of events (%)a | 476 (89%) | 494 (92%)
Median – months (95% CI) | 5.7 (5.5, 6.2) | 4.5 (4.2, 5.4)
Hazard Ratio (95% CI) | 0.79 (0.70, 0.90)
Stratified Log-rank p-value | <0.001
Abbreviations: CI = confidence interval.
a 73 of 476 events in CYRAMZA-treated patients and 64 of 494 events in placebo-treated patients were deaths.

Figure 5: Kaplan-Meier Curves for Overall Survival in RAISE

14.4 Hepatocellular Carcinoma

The efficacy of CYRAMZA was evaluated in REACH-2 (NCT02435433), a multinational, randomized, double-blind, placebo-controlled, multicenter study in patients with advanced HCC with AFP ≥400 ng/mL who had disease progression on or after prior sorafenib therapy or who were intolerant to sorafenib. Patients in REACH-2 were required to have ECOG PS of 0 or 1, Child-Pugh A, BCLC stage B and no longer amenable to locoregional therapy, or BCLC stage C. Patients were randomized (2:1) to receive CYRAMZA 8 mg/kg or placebo every 2 weeks as an intravenous infusion until disease progression or unacceptable toxicity. Randomization was stratified by geographic region, macrovascular invasion (yes versus no), and ECOG PS (0 versus 1). The major efficacy outcome measure was OS. Additional efficacy outcome measures included PFS and ORR based on investigator assessment.

A total of 292 patients were randomized, 197 to the CYRAMZA-treatment group and 95 to the placebo-treatment group. Baseline demographics and disease characteristics were similar between the arms. The median age was 64 years (range 26-88); 80% were men; 50% were Asian; 58% had ECOG PS 0; 35% had macrovascular invasion; 72% had extrahepatic spread; 17% were sorafenib intolerant, 37% had hepatitis B, 26% had hepatitis C, 24% had significant prior alcohol use, and 64% had prior locoregional therapy.

Efficacy results are shown in Table 15 and Figure 6.

Table 15: Efficacy Results in REACH-2
 | CYRAMZA + BSC N=197 | Placebo + BSC N=95
Overall Survival
Number of deaths (%) | 147 (75%) | 74 (78%)
Median – months (95% CI) | 8.5 (7.0, 10.6) | 7.3 (5.4, 9.1)
Hazard Ratio (95% CI) | 0.71 (0.53, 0.95)
Stratified Log-rank p-value | 0.020
Progression-free Survival
Number of events (%)a | 172 (87%) | 86 (91%)
Median – months (95% CI) | 2.8 (2.8, 4.1) | 1.6 (1.5, 2.7)
Hazard Ratio (95% CI) | 0.45 (0.34, 0.60)
Stratified Log-rank p-value | <0.0001
Overall Response Rateb
Rate – percent (95% CI) | 4.6% (1.7, 7.5) | 1.1% (0, 3.1)
Abbreviations: BSC = best supportive care; CI = confidence interval
a 26 of 172 events in CYRAMZA-treated patients and 9 of 86 events in placebo-treated patients were deaths.
b all responses were partial

Figure 6: Kaplan-Meier Curves for Overall Survival in REACH-2

16 HOW SUPPLIED/STORAGE AND HANDLING

CYRAMZA (ramucirumab) injection is a clear to slightly opalescent and colorless to slightly yellow, preservative-free solution supplied in single-dose vials.

- NDC 0002-7669-01
  100 mg/10 mL (10 mg/mL), individually packaged in a carton
- NDC 0002-7678-01
  500 mg/50 mL (10 mg/mL), individually packaged in a carton

Store vials in a refrigerator at 2°C to 8°C (36°F to 46°F) in the original carton to protect from light until time of use. Do not freeze or shake the vial.

17 PATIENT COUNSELING INFORMATION

Hemorrhage

Advise patients that CYRAMZA can cause severe bleeding. Advise patients to contact their health care provider for bleeding or symptoms of bleeding including lightheadedness [see Warnings and Precautions (5.1)].

Gastrointestinal Perforations

Advise patients to notify their health care provider for severe diarrhea, vomiting, or severe abdominal pain [see Warnings and Precautions (5.2)].

Impaired Wound Healing

Advise patients that CYRAMZA has the potential to impair wound healing. Instruct patients not to undergo surgery without first discussing this potential risk with their health care provider [see Warnings and Precautions (5.3)].

Arterial Thromboembolic Events

Advise patients of an increased risk of an arterial thromboembolic event [see Warnings and Precautions (5.4)].

Hypertension

Advise patients to undergo routine blood pressure monitoring and to contact their health care provider if blood pressure is elevated or if symptoms from hypertension occur including severe headache, lightheadedness, or neurologic symptoms [see Warnings and Precautions (5.5)].

Posterior Reversible Encephalopathy Syndrome

Advise patients to inform their health care provider if they develop neurological symptoms consistent with PRES (seizure, headache, nausea/vomiting, blindness, or altered consciousness) [see Warnings and Precautions (5.8)].

Embryo-Fetal Toxicity

Advise females of reproductive potential of the potential risk to a fetus. Advise females to inform their health care provider of a known or suspected pregnancy and to use effective contraception during CYRAMZA treatment and for 3 months after the last dose [see Warnings and Precautions (5.11), Use in Specific Populations (8.1, 8.3)].

Lactation

Advise women not to breastfeed during CYRAMZA treatment and for 2 months after the last dose [see Use in Specific Populations (8.2)].

Infertility

Advise females of reproductive potential that CYRAMZA may impair fertility [see Use in Specific Populations (8.3)].

Eli Lilly and Company, Indianapolis, IN 46285, USA

US License No. 1891

Copyright © 2014, 2025, Eli Lilly and Company. All rights reserved.

CYR-0020-USPI-20250819

PACKAGE LABELING

This section contains a representative sample of product package labeling. Product may be manufactured at other manufacturing sites.

PACKAGE CARTON –CYRAMZA 100 mg/10 mL single-use vial.

NDC 0002-7669-01

Cyramza®

(ramucirumab)

Injection

100 mg/10 mL

(10 mg/mL)

For Intravenous Infusion Only

Must Dilute Prior to Use

Single-Dose Vial

Discard Unused Portion

Keep Refrigerated

Rx only

www.cyramza.com

Lilly

CARTON FOR US ORIGIN

CARTON FOR IRELAND ORIGIN

PACKAGE LABEL

PACKAGE CARTON – CYRAMZA 500 mg/50mL single-use vial.

NDC 0002-7678-01

Cyramza®

(ramucirumab)

Injection

500 mg/50 mL

(10 mg/mL)

For Intravenous Infusion Only

Must Dilute Prior to Use

Single-Dose Vial

Discard Unused Portion

Keep Refrigerated

Rx only

www.cyramza.com

Lilly

CARTON FOR US ORIGIN

CARTON FOR IRELAND ORIGIN